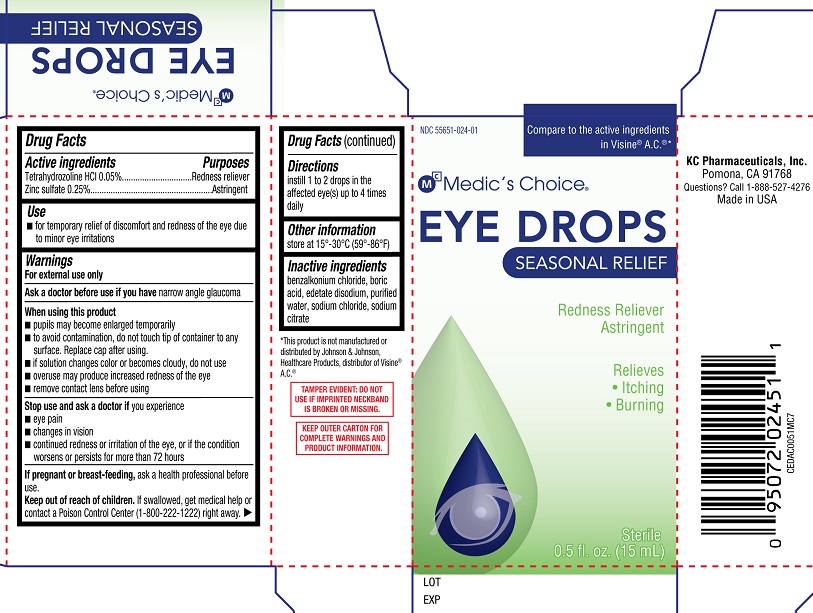 DRUG LABEL: Medics Choice Eye Drops Seasonal Relief
NDC: 55651-024 | Form: SOLUTION/ DROPS
Manufacturer: KC Pharmaceuticals, Inc.
Category: otc | Type: HUMAN OTC DRUG LABEL
Date: 20251230

ACTIVE INGREDIENTS: ZINC SULFATE 2.5 mg/1 mL; TETRAHYDROZOLINE HYDROCHLORIDE 0.5 mg/1 mL
INACTIVE INGREDIENTS: BENZALKONIUM CHLORIDE; WATER; SODIUM CHLORIDE; BORIC ACID; EDETATE DISODIUM; SODIUM CITRATE

Medic's Choice Eye Drops Seasonal Relief

Active ingredients

Tetrahydrozoline HCl 0.05%

Zinc sulfate 0.25%

Purposes

Tetrahydrozoline HCl.....Redness reliever

Zinc sulfate...............Astringent

Use

■ for temporary relief of discomfort and redness of the eye due to minor eye irritations

Warnings

For external use only

Ask a doctor before use if you have narrow angle glaucoma

When using this product

■ pupils may become enlarged temporarily

■ to avoid contamination, do not touch tip of container to any surface. Replace cap after using.

■ if solution changes color or becomes cloudy, do not use

■ overuse may produce increased redness of the eye

■ remove contact lens before using

Stop use and ask a doctor if you experience

■ eye pain

■ changes in vision

■ continued redness or irritation of the eye, or if the condition worsens or persists for more than 72 hours

PREGNANCY OR BREAST FEEDING

If pregnant or breast-feeding, ask a health professional before use.

Keep out of reach of children. If swallowed, get medical help or contact a Poison Control Center

(1-800-222-1222) right away.

Directions

instill 1 to 2 drops in the affected eye(s) up to 4 times daily

Other information

store at 15°-30°C (59°-86°F)

Inactive ingredients

benzalkonium chloride, boric acid, edetate disodium, purified water, sodium chloride, sodium citrate